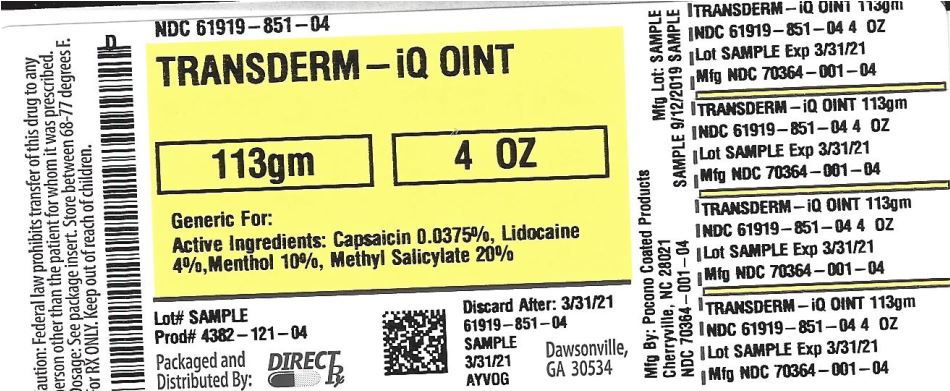 DRUG LABEL: TRANSDERM-IQ
NDC: 61919-851 | Form: OINTMENT
Manufacturer: Direct_Rx
Category: otc | Type: HUMAN OTC DRUG LABEL
Date: 20190911

ACTIVE INGREDIENTS: CAPSAICIN 0.0375 g/100 g; MENTHOL, UNSPECIFIED FORM 10 g/100 g; METHYL SALICYLATE 20 g/100 g; LIDOCAINE 4 g/100 g
INACTIVE INGREDIENTS: WATER; GLYCERYL MONOSTEARATE; STEARIC ACID; GLYCERIN; TROLAMINE; CARBOMER HOMOPOLYMER TYPE B (ALLYL SUCROSE CROSSLINKED); CETYL ALCOHOL; POLYOXYL 20 CETOSTEARYL ETHER; ALOE VERA LEAF; DIMETHICONE; ISOPROPYL MYRISTATE; CARBOXYPOLYMETHYLENE; METHYLPARABEN; PROPYLPARABEN; EDETATE DISODIUM ANHYDROUS; MINERAL OIL; PROPYLENE GLYCOL; PETROLATUM; DIAZOLIDINYL UREA; IODOPROPYNYL BUTYLCARBAMATE

TRANSDERM-IQ

WARNINGS

For external use only

use only as directed. Read and follow all directions and warnings on this carton.
avoid contact with eyes and mucous membranes
do not use at the same time as other topical analgesics
do not use on open wounds, cuts, damaged or infected skin
do not use with bandage or heating pad.

Stop use and ask a doctor if

condition worsens
symptoms persist for more than 7 days or clear up and occur again within a few days

If pregnant or breast-feeding or if you have sensitive skin, ask a health professional before use

INACTIVE INGREDIENT

Purified Water, Mineral Oil, Isopropyl Myristate, Cetyl Alcohol, Glycerol Monostearate, Stearic Acid, Glycerin, Propylene Glycol, Cetereth-20, Carbomer, Aloe Vera, Disodium EDTA, Dimethicone, Petrolatum, Methylparaben, Triethanolamine, Diazolidinyl Urea, Iodopropynyl Butylcarbamate, Propylparaben, Beeswax, Sodium Carbomer, Phenonip, Triethanolamine.

New Hands Free Applicator

(Quad-5 Ball Roller)

Long Lasting and Soothing Deep Penetrating Action

KEEP OUT OF REACH OF CHILDREN

If swallowed, get medical help or contact Poison Control Center right away

PURPOSE

Topical analgesic

ACTIVE INGREDIENT

Capsaicin 0.0375%

Lidocaine 4%

Menthol 10%

Methyl Salicylate 20%

INDICATIONS AND USAGE

Temporary relief of minor aches and pains of muscles and joints associated with:• simple backache • arthritis • muscle strains • sprains • bruises

DOSAGE AND ADMINISTRATION

Adults 18 years and children 12 years and older:

apply product directly to affected area
product may be used as necessary, but should not be used more than four times per day
wash hands immediately afterwards.